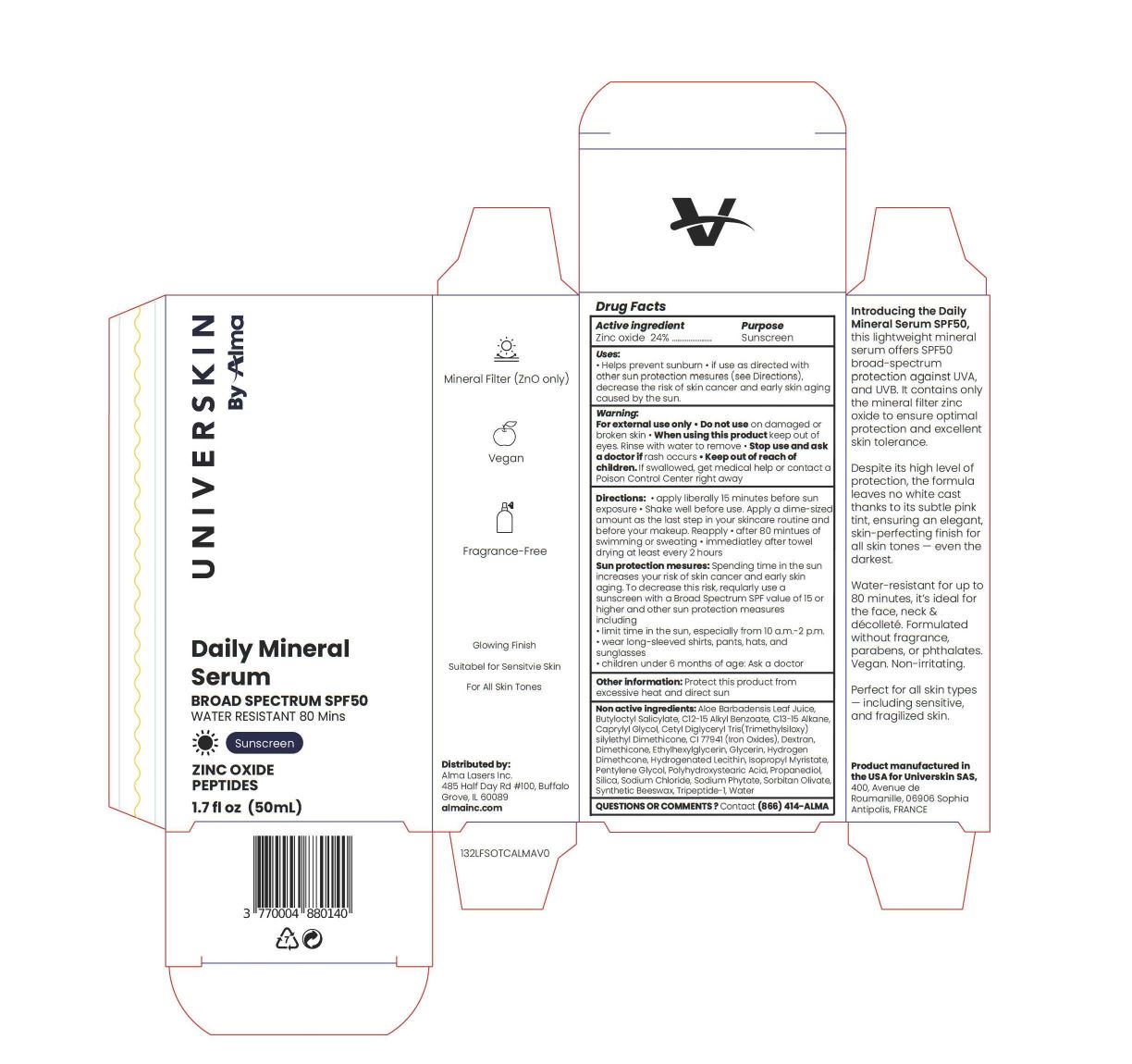 DRUG LABEL: Universkin by Alma Daily Mineral Serum Broad Spectrum SPF50
NDC: 87279-1001 | Form: LOTION
Manufacturer: UNIVERSKIN
Category: otc | Type: HUMAN OTC DRUG LABEL
Date: 20251213

ACTIVE INGREDIENTS: ZINC OXIDE 24 g/100 mL
INACTIVE INGREDIENTS: TRIPEPTIDE-1; C13-15 ALKANE; ETHYLHEXYLGLYCERIN; SORBITAN OLIVATE; HYDROGEN DIMETHICONE (40 CST); DEXTRAN 70; SYNTHETIC BEESWAX; BUTYLOCTYL SALICYLATE; CETYL DIGLYCERYL TRIS(TRIMETHYLSILOXY)SILYLETHYL DIMETHICONE (3500 MM2/S); PENTYLENE GLYCOL; GLYCERIN; ALOE BARBADENSIS LEAF JUICE; C12-15 ALKYL BENZOATE; CI 77491; HYDROGENATED SOYBEAN LECITHIN; CAPRYLYL GLYCOL; SODIUM CHLORIDE; ISOPROPYL MYRISTATE; POLYHYDROXYSTEARIC ACID (2300 MW); DIMETHICONE; SILICA; CI 77499; WATER; SODIUM PHYTATE; PROPANEDIOL

Universkin by Alma Daily Mineral Serum Broad Spectrum SPF50

Active Ingredient

Zinc Oxide 24%

Purpose

Sunscreen

Uses

- Helps prevent sunburn
- If use as directed with other sun protection measures (see Directions), decrease the risk of skin cancer and early skin aging caused by the sun.

Warnings

For external use only

- Do not use on damaged or broken skin
- When using this product keep out of eyes. Rinse with water to remove.
- Stop use and ask a doctor if rash occurs

Keep out of reach of children. If swallowed, get medical help or contact a Poison Control Center right away.

Directions:

- apply liberally 15 minutes behore sun exposure
- Shake well before use. Apply a dime-sized amount as the last step in your skincare routine and before your makeup.

Reapply:

- after 80 minutes of swimming or sweating
- immediately after towel drying at least every 2 hours

Sun Protection Measures. Spending time in the sun increases your risk of skin cancer and early skin aging. To decrease this risk, regularly use a sunscreen with a Broad Spectrum SPF value of 15 or higher and other sun protection measures including:

- limit time in the sun, especially from 10 a.m. - 2 p.m.
- wear long-sleeved shirts, pants, hats, and sunglasses
- children under 6 months of age: Ask a doctor.

Other Information

Other Information: Protect this product from excessive heat and direct sun

Inactive Ingredients

Non active ingredients: Aloe Barbadensis Leaf Juice,

Butyloctyl Salicylate, C12-15 Alkyl Benzoate, C13-15 Alkane,

Caprylyl Glycol, Cetyl Diglyceryl tris(Trimethylsiloxy)

silylethyl Dimethicone, CI 77941 (Iron Oxides), Dextran,

Dimethicone, Ethylhexylglycerin, Glycerin, Hydrogen

Dimethcone, Hydrogenated Lecithin, Isopropyl Myristate,

Pentylene Glycol, Polyhydroxystearic Acid, Propanediol,

Silica, Sodium Chloride, Sodium Phytate, Sorbitan Olivate,

Synthetic Beeswax, Tripeptide-1, Water

Package Label. Principal Display Panel

UNIVERSKIN By Alma

Daily Mineral

Serum

BROAD SPECTRUM SPF50

WATER RESISTANT 80 Mins

Sunscreen

ZINC OXIDE

PEPTIDES

1.7 fl oz (50mL)